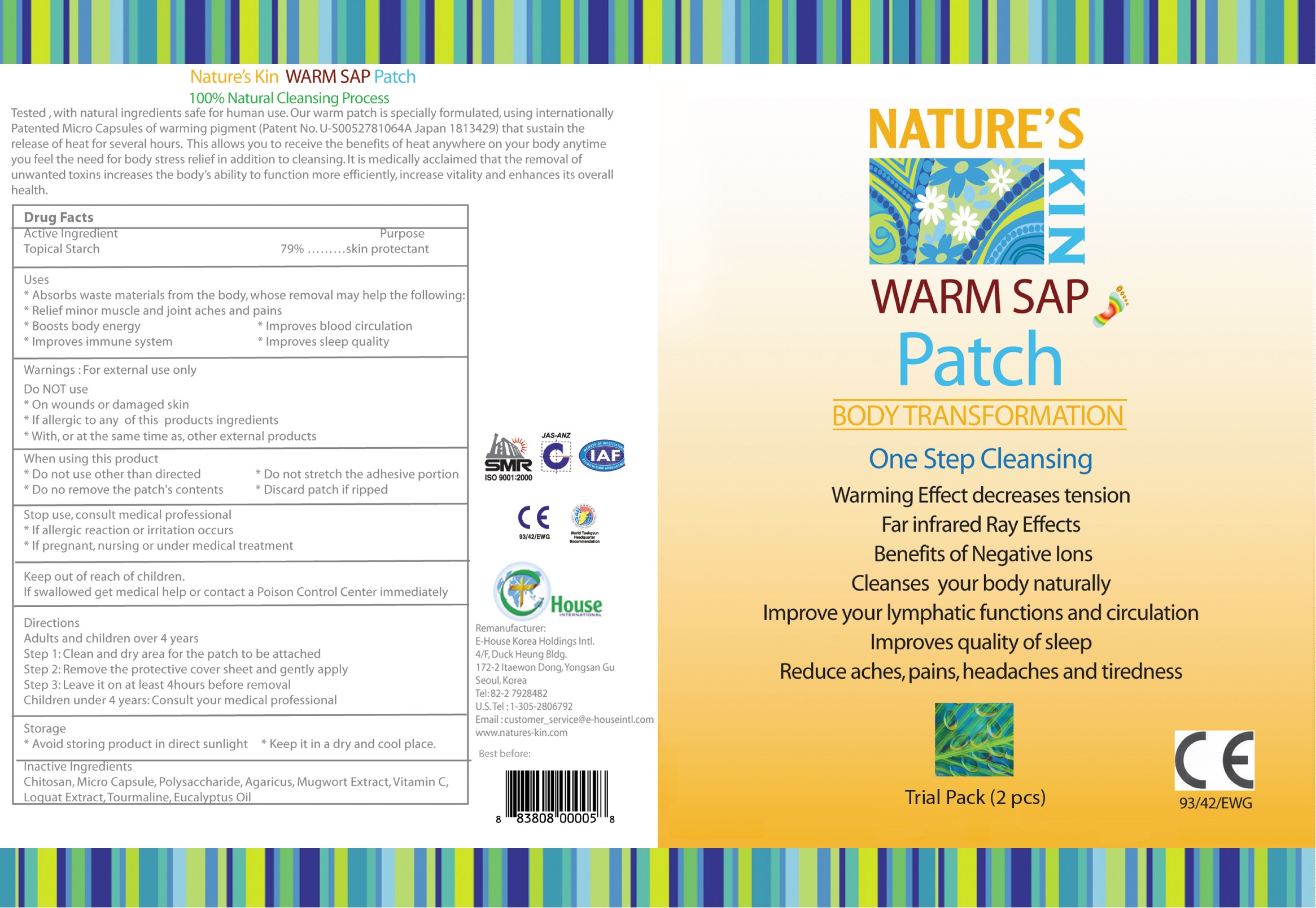 DRUG LABEL: Warm Sap Patch
NDC: 50387-200 | Form: POULTICE
Manufacturer: E-House Korea Holdings International
Category: otc | Type: HUMAN OTC DRUG LABEL
Date: 20100131

ACTIVE INGREDIENTS: STARCH, CORN 3.16 g/4 g

Active Ingredient:

Topical Starch

When using this product:
- Do not use other than directed
- Do not stretch the adhesive portion
- Do not remove the patch's contents
- Discard patch if ripped

Do Not Use:
- on wounds or damaged skin
- if allergic to any of this product's ingredients
- With or at the same time as other external products

Stop Use and Consult Medical Professional
- if allergic reaction or irritation occurs
- if pregnant, nursing or under medical treatment

Keep out of reach of children
If swallowed, get medical help or contact a Poison Control Center immediately

STORAGE AND HANDLING

Avoid storing product in direct sunlight. Keep it in a dry and cool place.

WARNINGS

For external use only

DESCRIPTION

How To Use:
Apply to arches of the feet, center of the hands, toes and fingers since many of the main bodily organs connect at these locations. The patch may be used at any time but is usually most convenient just prior to bed. For localized treatment, place the patch on any aching, sprained or sore area.

Inactive Ingredients:
Chitosan, Micro Capsule, Polysaccharide, Agaricus, Mugwort Extract, Vitamin C, Loquat Extract, Tourmaline, Eucalyptus Oil

Directions:
Adults and children over 4 years
Step 1: Clean and dry area for the patch to be attached
Step 2: Remove the protective cover sheet and gently apply
Step 3: Leave it on at least 4 hours before removal
Children under 4 years, consult your medical professional